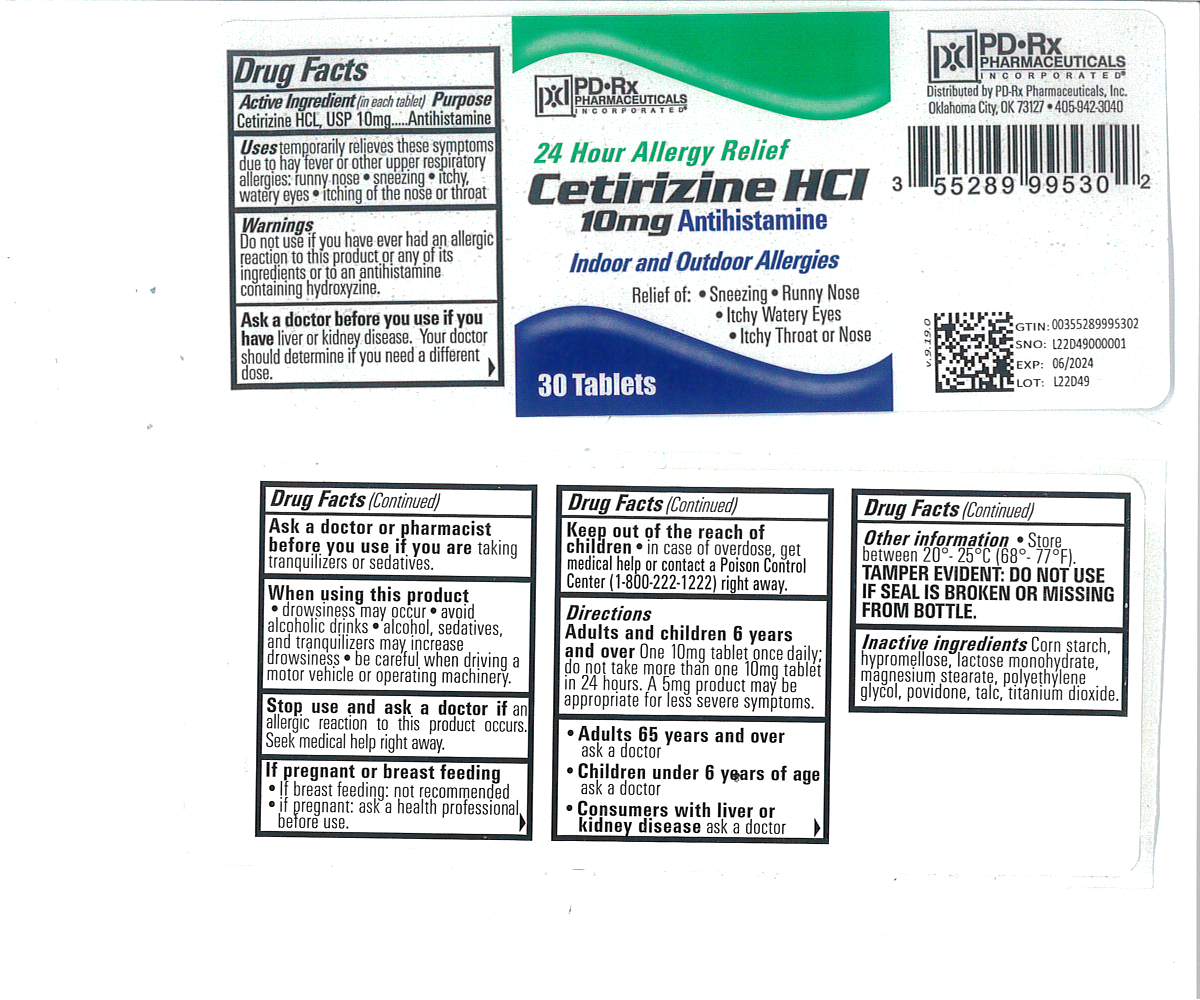 DRUG LABEL: Cetirizine Hydrochloride
NDC: 55289-995 | Form: TABLET
Manufacturer: PD-Rx Pharmaceuticals, Inc.
Category: otc | Type: HUMAN OTC DRUG LABEL
Date: 20251020

ACTIVE INGREDIENTS: CETIRIZINE HYDROCHLORIDE 10 mg/1 1
INACTIVE INGREDIENTS: POVIDONE, UNSPECIFIED; LACTOSE MONOHYDRATE; MAGNESIUM STEARATE; STARCH, CORN; TALC; TITANIUM DIOXIDE; HYPROMELLOSE, UNSPECIFIED; POLYETHYLENE GLYCOL, UNSPECIFIED

Cetirizine Hydrochloride

Drug Facts

Active ingredient (in each tablet)

Cetirizine HCl, USP 10 mg

Purpose

Antihistamine

Uses

temporarily relieves these symptoms due to hay fever or other upper respiratory allergies:

- runny nose
- sneezing
- itchy, watery eyes
- itching of the nose or throat

Warnings

Do not use if you have ever had an allergic reaction to this product or any of its ingredients or to an antihistamine containing hydroxyzine.

Ask a doctor before use if you have liver or kidney disease. Your doctor should determine if you need a different dose.

Ask a doctor or pharmacist before use if you are taking tranquilizers or sedatives.

When using this product

- drowsiness may occur
- avoid alcoholic drinks
- alcohol, sedatives, and tranquilizers may increase drowsiness
- be careful when driving a motor vehicle or operating machinery

Stop use and ask a doctor if an allergic reaction to this product occurs. Seek medical help right away.

If pregnant or breast-feeding

- if breast-feeding: not recommended
- if pregnant: ask a health professional before use.

Keep out of reach of children. In case of overdose, get medical help or contact a Poison Control Center right away (1-800-222-1222).

Directions

adults and children 6 years and over | one 10 mg tablet once daily; do not take more than one 10 mg tablet in 24 hours. A 5 mg product may be appropriate for less severe symptoms.
adults 65 years and over | ask a doctor
children under 6 years of age | ask a doctor
consumers with liver or kidney disease | ask a doctor

Other information

- TAMPER EVIDENT: DO NOT USE IF SAFETY SEAL IS BROKEN OR MISSING FROM BOTTLE.
- store between 20° to 25° C (68° to 77° F)

Inactive ingredients

corn starch, hypromellose, lactose monohydrate, magnesium stearate, polyethylene glycol, povidone, talc, titanium dioxide

Questions?

call 1-800-406-7984

HOW SUPPLIED

Cetirizine HCL 10mg:

10 mg white, rectangle (rounded-off), tablets, debossed "RI52" on obverse and plain on reverse. They are available as follows:

Bottles of 7: NDC 55289-995-07

Bottles of 10: NDC 55289-995-10

Bottles of 30: NDC 55289-995-30

Bottles of 90: NDC 55289-995-90

PRINCIPAL DISPLAY PANEL - 10 mg Tablet Bottle Label

Cetirizine HCl Tablets, USP 10 mg
ANTIHISTAMINE